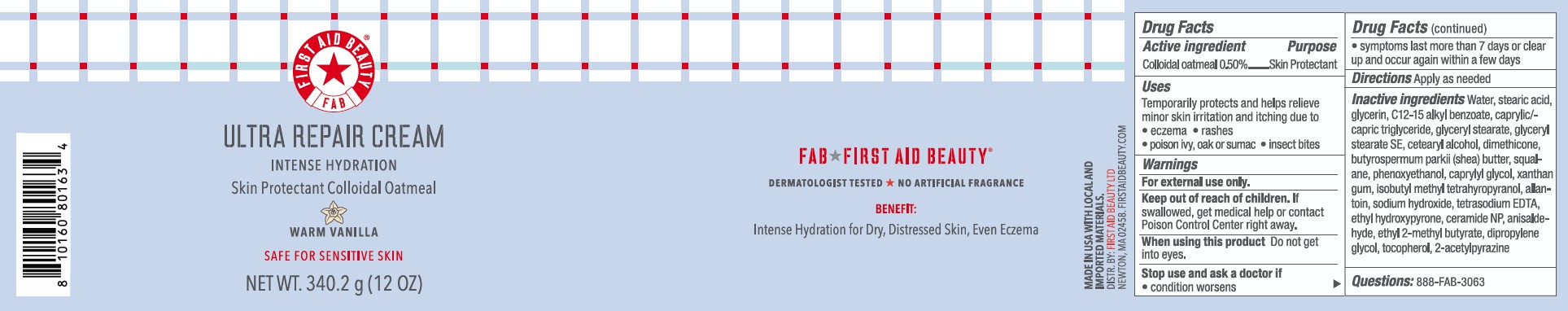 DRUG LABEL: First Aid Beauty FAB Ultra Repair Intense Hydration Skin Protectant Warm Vanilla
NDC: 84126-213 | Form: CREAM
Manufacturer: The Procter & Gamble Manufacturing Company
Category: otc | Type: HUMAN OTC DRUG LABEL
Date: 20251209

ACTIVE INGREDIENTS: OATMEAL 0.5 g/100 g
INACTIVE INGREDIENTS: 2-ACETYLPYRAZINE; ETHYL HYDROXYPYRONE; DIPROPYLENE GLYCOL; TOCOPHEROL; CETEARYL ALCOHOL; SQUALANE; DIMETHICONE; TETRASODIUM EDTA; GLYCERYL STEARATE SE; C12-15 ALKYL BENZOATE; CAPRYLYL GLYCOL; SODIUM HYDROXIDE; PHENOXYETHANOL; BUTYROSPERMUM PARKII (SHEA) BUTTER; WATER; GLYCERIN; ALLANTOIN; GLYCERYL STEARATE; CAPRYLIC/CAPRIC TRIGLYCERIDE; STEARIC ACID; XANTHAN GUM; CERAMIDE NP; ISOBUTYL METHYL TETRAHYDROPYRANOL; ETHYL 2-METHYLBUTYRATE; ANISALDEHYDE

First Aid Beauty FAB Ultra Repair Cream Skin Protectant Vanilla

Drug Facts

Active ingredients

Colloidal Oatmeal 0.5%

Purpose

Skin Protectant

Uses

- Temporarily protects and helps relieve minor skin irritation and itching due to eczema, rashes, poison ivy, oak or sumac, insect bites

Warnings

For external use only.

Keep out of reach of children. If swallowed, get medical help or contact a Poison Control Center right away.

WHEN USING

Do not get into eyes.

Stop use and ask a doctor if condition worsens, symptoms last more than 7 days or clear up and occur again within a few days

Directions

Apply as needed

INACTIVE INGREDIENT

Water, stearic acid, glycerin, c12-15 alkyl benzoate, caprylic/capric triglyceride, glyceryl stearate, glyceryl stearate SE, cetearyl alcohol, dimethicone, butyrospermum parkii (shea) butter, squalene, phenoxyethanol, caprylyl glycol, xanthan gum, isobutyl methyl tetrahyropyranol, allantoin, sodium hydroxide, tetrasodium EDTA, ethyl hydroxypyrone, ceramide NP, anisaldehyde, etheyl 2-methyl butyrate, dipropylene glycol, tocopherol, 2-acetylpyrazine

Questions:

888-FAB-3063

MADE IN USA

FIRST AID BEAUTY LTD

NEWTON, MA 02458

WWW.FIRSTAIDBEAUTY.COM

PRINCIPAL DISPLAY PANEL - 14.0 oz (396.8 g)

First Aid Beauty

FAB

Ultra Repair® Cream

Intense Hydration

Skin Protectant Colloidal Oatmeal

Warm Vanilla

FIrst Aid Beauty ®

Net Wt. 12.0 oz (340.2 g)